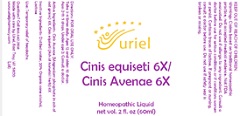 DRUG LABEL: Cinis equiseti 6X/Cinis Avenae 6X
NDC: 48951-3244 | Form: LIQUID
Manufacturer: Uriel Pharmacy Inc.
Category: homeopathic | Type: HUMAN OTC DRUG LABEL
Date: 20210819

ACTIVE INGREDIENTS: MAGNESIUM PHOSPHATE, TRIBASIC, PENTAHYDRATE 6 [hp_X]/1 mL; EQUISETUM ARVENSE TOP 6 [hp_X]/1 mL
INACTIVE INGREDIENTS: ALCOHOL; WATER; LACTOSE, UNSPECIFIED FORM

Cinis Equiseti 6X/Cinis Avenae 6X

INDICATIONS AND USAGE

Directions: FOR ORAL USE ONLY.

DOSAGE AND ADMINISTRATION

Take 3-4 times daily. Ages 12 and older: 10 drops. Ages 2-11: 5 drops. Under age 2: Consult a doctor.

ACTIVE INGREDIENT

Active Ingredients: Cinis Avenae (Magnesium phosphate in ash of oat grains) 6X, Cinis equiseti (Ash of horsetail herb) 6X

INACTIVE INGREDIENT

Inactive Ingredients: Distilled water, 20% Organic cane alcohol, Lactose

PURPOSE

Use: Temporary relief of headache.

KEEP OUT OF REACH OF CHILDREN.

WARNINGS

Warnings: Claims based on traditional homeopathic practice, not accepted medical evidence. Not FDA evaluated. Do not use if allergic to any ingredient. Consult a doctor before use for serious conditions or if conditions worsen or persist. Contains traces of lactose.
If pregnant or nursing, consult a doctor before use. Do not use if safety seal is broken or missing.

Questions? Call 866.642.2858
Made with care by Uriel, East Troy, WI 53120
www.urielpharmacy.com Lot: